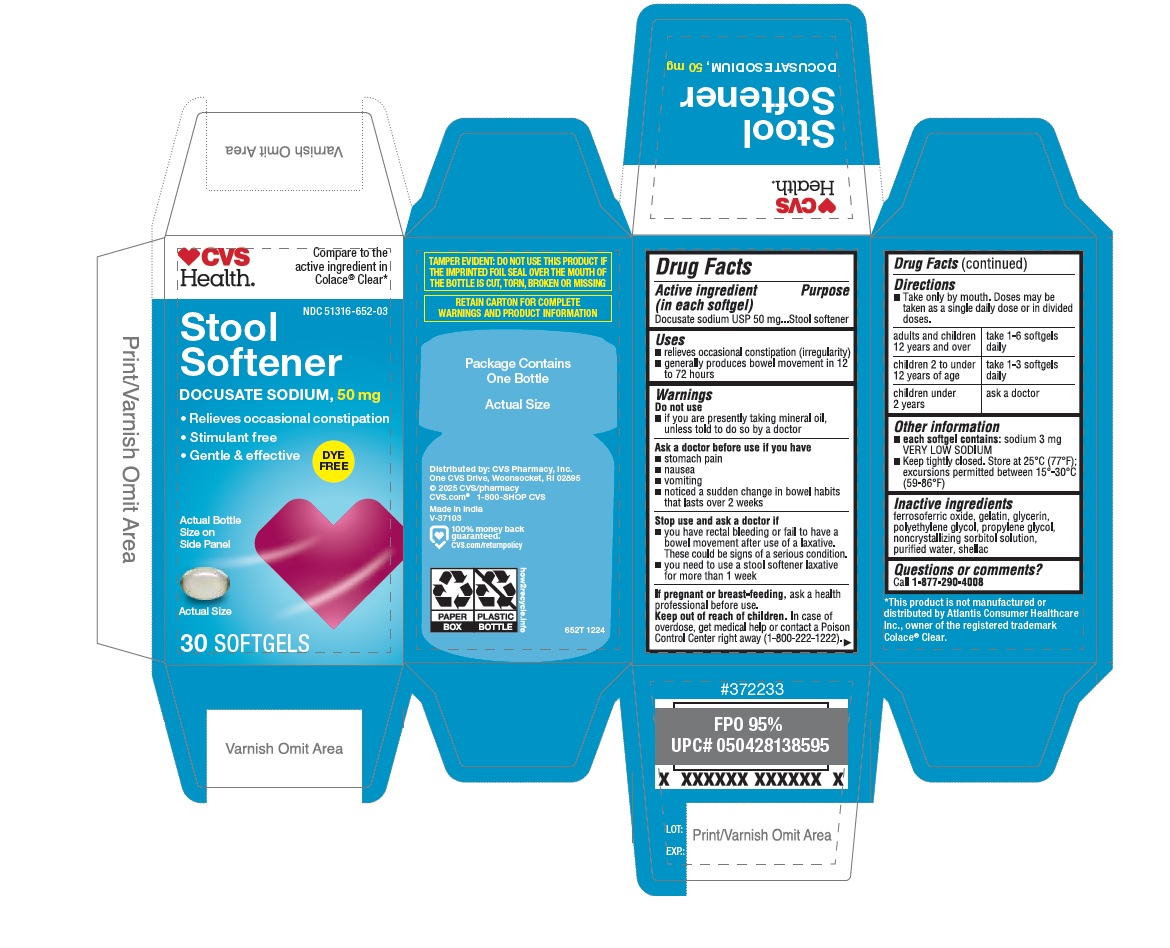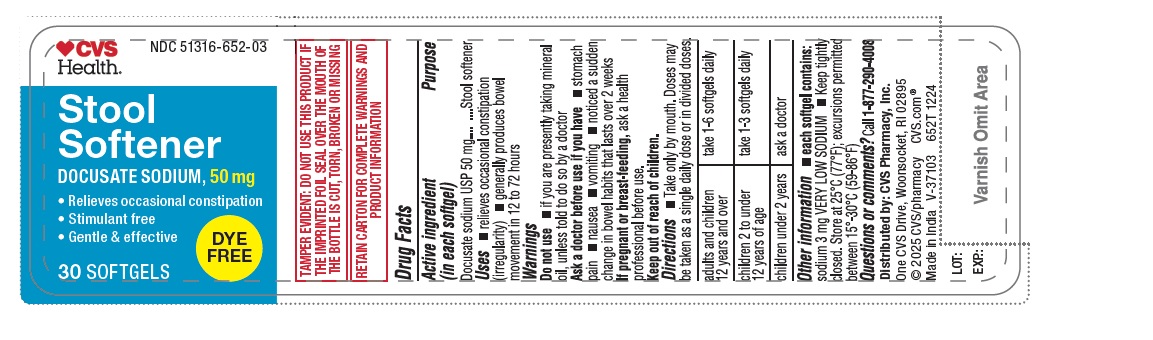 DRUG LABEL: Docusate Sodium softgels 50mg (Dye Free)	
NDC: 51316-652 | Form: CAPSULE, LIQUID FILLED
Manufacturer: CVS Pharmacy
Category: otc | Type: HUMAN OTC DRUG LABEL
Date: 20250204

ACTIVE INGREDIENTS: DOCUSATE SODIUM 50 mg/1 1
INACTIVE INGREDIENTS: NONCRYSTALLIZING SORBITOL SOLUTION; WATER; GELATIN; PROPYLENE GLYCOL; GLYCERIN; POLYETHYLENE GLYCOL, UNSPECIFIED; FERROSOFERRIC OXIDE; SHELLAC

CVS 652T DOCUSATE SODIUM 50MG SOFTGEL(Dye-free)

Drug Facts

Active ingredient (in each softgel)

Docusate sodium USP 50 mg

Purpose

Stool softener

Uses

- relieves occasional constipation (irregularity)
- generally produces bowel movement in 12 to 72 hours

Warnings

Do not use

- if you are presently taking mineral oil, unless told to do so by a doctor

Ask a doctor before use if you have

- stomach pain
- nausea
- vomiting
- noticed a sudden change in bowel habits that lasts over 2 weeks

Stop use and ask a doctor if

- you have rectal bleeding or fail to have a bowel movement after use of a laxative. These could be signs of a serious condition.
- you need to use a stool softener laxative for more than 1 week

PREGNANCY OR BREAST FEEDING

If pregnant or breast-feeding, ask a health professional before use.

Keep out of reach of children. In case of overdose, get medical help or contact a Poison Control Center right away (1-800-222-1222).

Directions

- Take only by mouth. Doses may be taken as a single daily dose or in divided doses.

adults and children; 12 years and over | take 1-6 softgels daily
children 2 to; under 12 years of age | take 1-3 softgels daily
children under 2 years | ask a doctor

Other information

- each softgel contains: sodium 3 mg VERY LOW SODIUM
- Keep tightly closed. Store at 25°C (77°F); excursions permitted between 15°-30°C (59-86°F)

INACTIVE INGREDIENT

Inactive ingredients ferrosoferric oxide, gelatin, glycerin, polyethylene glycol, propylene glycol, noncrystallizing sorbitol solution, purified water, shellac

Questions or comments? Call 1-877-290-4008